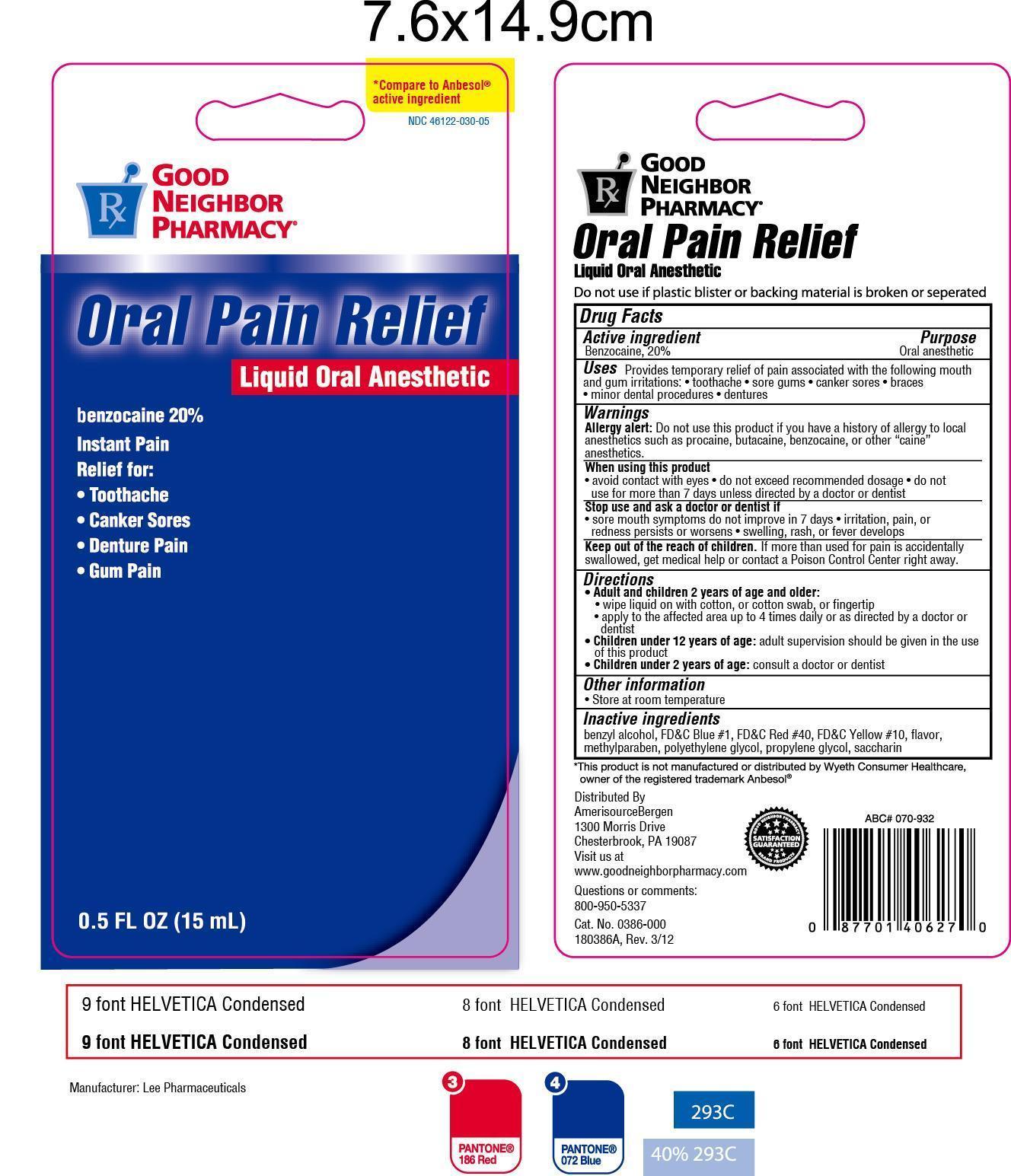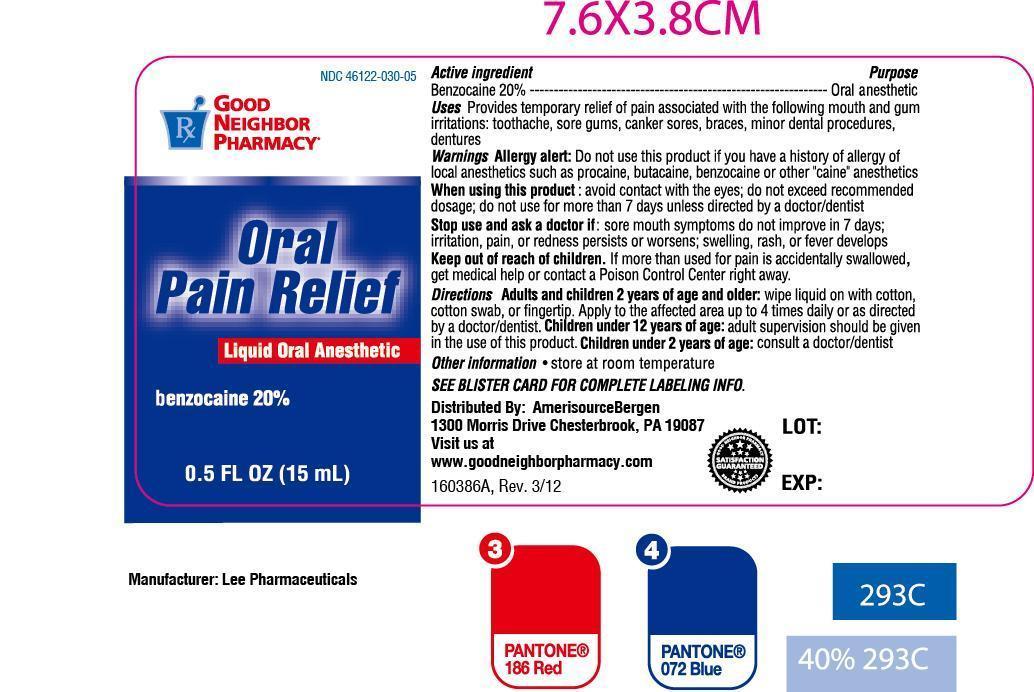 DRUG LABEL: Good Neighbor Pain Relief
NDC: 46122-030 | Form: LIQUID
Manufacturer: AmerisourceBergen Drug Corporation (Good Neighbor Pharmacy)
Category: otc | Type: HUMAN OTC DRUG LABEL
Date: 20130627

ACTIVE INGREDIENTS: BENZOCAINE 200 mg/1 mL
INACTIVE INGREDIENTS: BENZYL ALCOHOL; D&C YELLOW NO. 10; FD&C BLUE NO. 1; FD&C RED NO. 40; METHYLPARABEN; POLYETHYLENE GLYCOL 400; PROPYLENE GLYCOL; SACCHARIN

Drug Facts

Active ingredient

Benzocaine, 20%

Purpose

Oral anesthetic

Uses

Provides temporary relief of pain associated with the following mouth and gum irritations:

- toothache
- sore gums
- canker sores
- braces
- minor dental procedures
- dentures

Warnings

Allergy alert: Do not use this product if you have a history of allergy to local anesthetics such as procaine, butacaine, benzocaine, or other "caine" anesthetics.

When using this product

- avoid contact with eyes
- do not exceed recommended dosage
- do not use for more than 7 days unless directed by a doctor or dentist

Stop use and ask a doctor or dentist if

- sore mouth symptoms do not improve in 7 days
- irritation, pain, or redness persists or worsens
- swelling, rash, or fever develops

Keep out of reach of children

- If more than used for pain is accidentally swallowed, get medical help or contact a Poison Control Center right away

Directions

- Adults and children 2 years of age and older:
- wipe liquid on with cotton, or cotton swab, or finger tip.
- apply to the affected area up to 4 times daily of as directed by a doctor or dentist.
- Children under 12 years of age: adult supervision should be given in the use of this product.
- Children under 2 years of age: consult a doctor or dentist.

Inactive ingredients

Benzyl alcohol, FD&C Blue #1, FD&C Red #40, D&C yellow #10, Flavor, Methylparaben, Polyethylene Glycol, Propylene Glycol, Saccharin